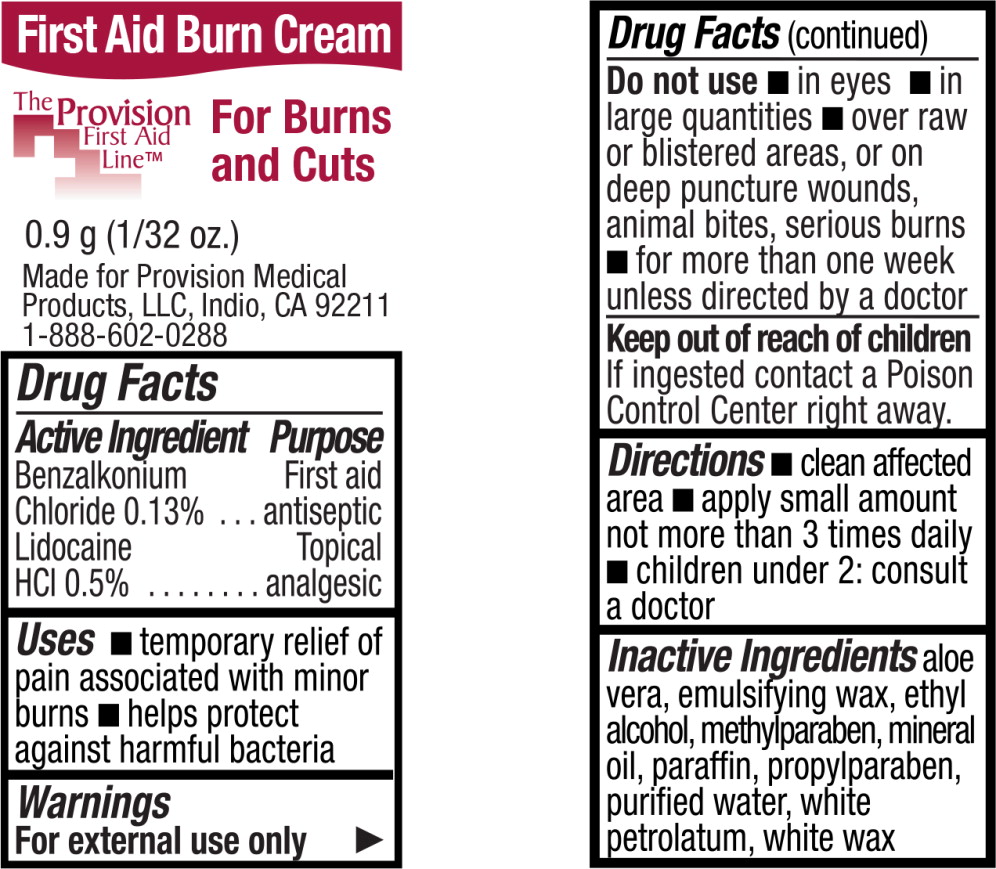 DRUG LABEL: Lidocaine Hydrochloride
NDC: 69103-5000 | Form: GEL
Manufacturer: Provision Medical
Category: otc | Type: HUMAN OTC DRUG LABEL
Date: 20131111

ACTIVE INGREDIENTS: Lidocaine Hydrochloride 20 mg/1 g
INACTIVE INGREDIENTS: aloe vera leaf; propylene glycol; diazolidinyl urea; water; menthol; .alpha.-tocopherol acetate; trolamine

Drug Facts

Active Ingredient

Benzalkonium

Chloride 0.13% ...

Lidocaine

HCl 0.5%

Purpose

First aid

antiseptic

Topical

analgesic

Uses

- temporary relief of pain associated with minor burns
- helps protect against harmful bacteria

Warnings

For external use only

Do not use

- in eyes
- in large quantities
- over raw or blistered areas, or on deep puncture wounds, animal bites, serious burns
- for more than one week unless directed by a doctor

Keep out of reach of children

If ingested contact a Poison Control Center right away.

Directions

- clean affected area
- apply small amount not more than 3 times daily
- children under 2: consult a doctor

Inactive Ingredients

aloe vera, emulsifying wax, ethyl alcohol, methylparaben, mineral oil, paraffin, propylparaben, purified water, white petrolatum, white wax

Principal Display Panel – 0.9 g Packet Label

First Aid Burn Cream

The Provision
First Aid
Line™

For Burns
and Cuts

0.9 g (1/32 oz.)